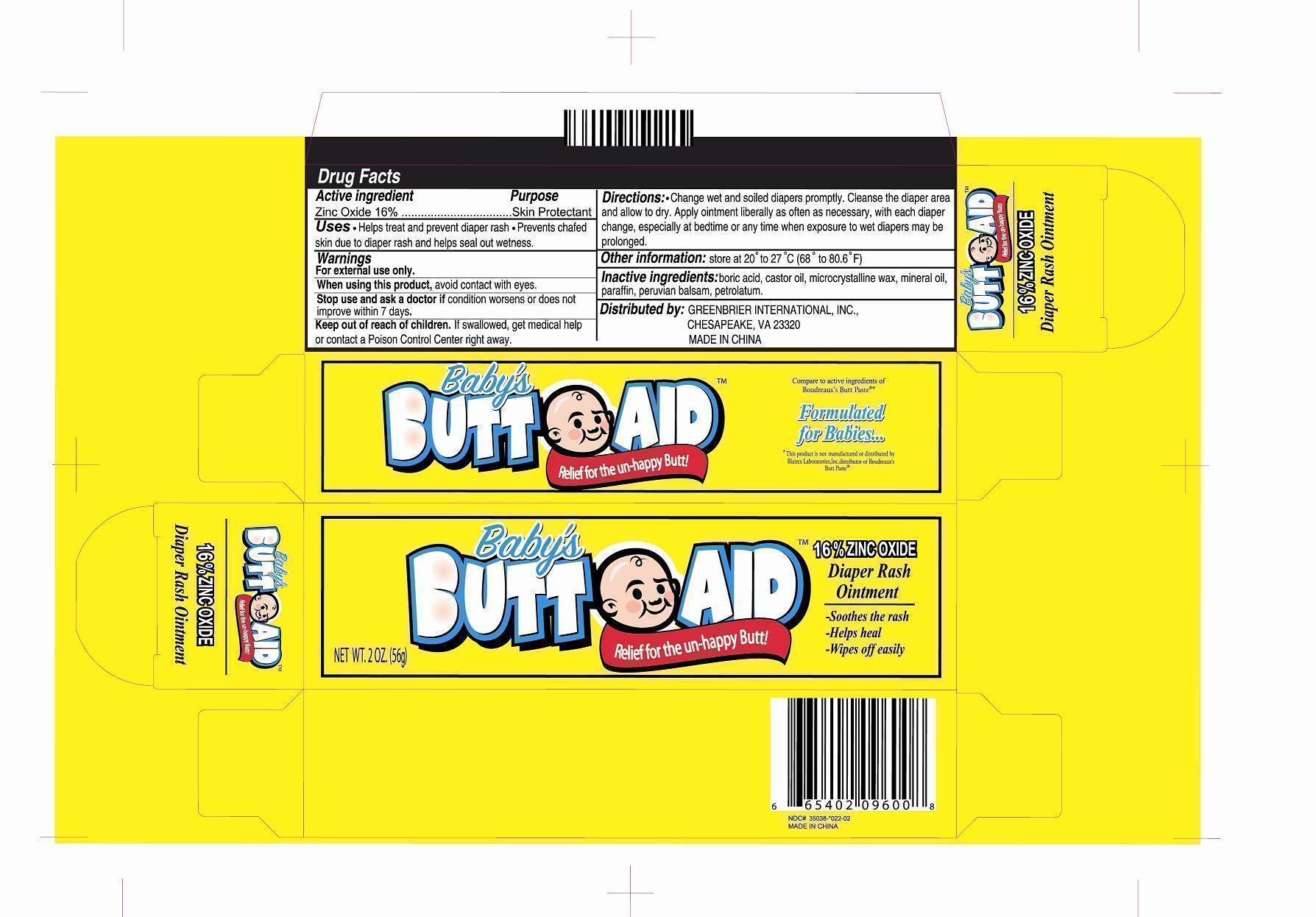 DRUG LABEL: BABYS BUTT AID
NDC: 33992-1306 | Form: OINTMENT
Manufacturer: GREENBRIER INTERNATIONAL INC
Category: otc | Type: HUMAN OTC DRUG LABEL
Date: 20140101

ACTIVE INGREDIENTS: ZINC OXIDE 16 g/100 g
INACTIVE INGREDIENTS: BORIC ACID 2 g/100 g; CASTOR OIL 30 g/100 g; MINERAL OIL 31.5 g/100 g; PARAFFIN 10 g/100 g; PETROLATUM 10 g/100 g

DRUG FACTS

For external use only

- flammable, keep away from fire and flame
- will produce serious gastric disturbances if taken internally

Ask a doctor before use if you have deep puncture wounds or serious burns

When using this product

- do not get into eyes or mucous membranes
- use only in a well-ventilated area

Stop use and ask a doctor if condition persists or gets worse.

Keep out of reach of children. In case of an accidental ingestion, contact a Poison Control Center immediately.

Active ingredient

Zinc Oxide 16%

Purpose

Skin Protectant

Uses

- Helps treat and prevent diaper rash
- Prevents chafed skin due to diaper rash and helps seal out wetness.

Warnings

For external use only.

When using this product, avoid contact with eyes.

Stop use and ask a doctor if condition worsens or does not improve within 7 days.

Keep out of reach of children. If swallowed, get medical help or contact a Poison Control Center right away.

Directions

Change wet and soiled diapers promptly. Cleanse the diaper area and allow to dry. Apply ointment liberally as often as necessary, with each diaper change, especially at bedtime or any time when exposure to wet diapers may be prolonged.

Other information

store at 20 to 27 C (68 to 80.6 F)

Inactive ingredients

boric acid, castor oil, microcrystalline wax, mineral oil, paraffin, peruvian balsam, petrolatum

PACKAGE LABEL

Enter section text here